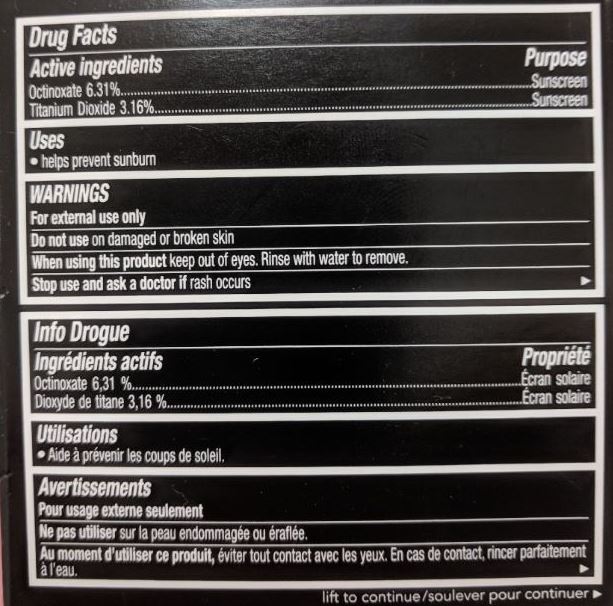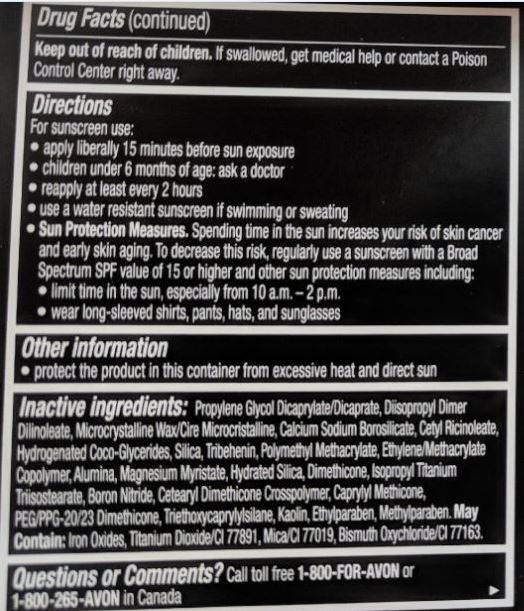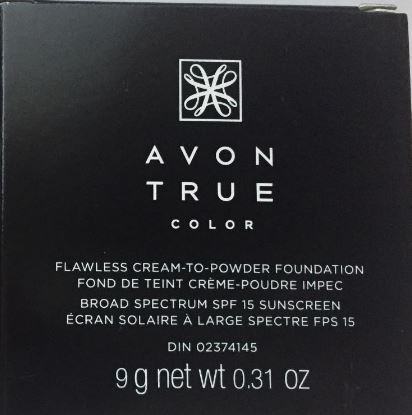 DRUG LABEL: Avon True Color
NDC: 71110-0007 | Form: CREAM
Manufacturer: Avon Products, Inc.
Category: otc | Type: HUMAN OTC DRUG LABEL
Date: 20181214

ACTIVE INGREDIENTS: OCTINOXATE 63.1 mg/1 g; TITANIUM DIOXIDE 31.6 mg/1 g
INACTIVE INGREDIENTS: TRIETHOXYCAPRYLYLSILANE; MICA; BISMUTH OXYCHLORIDE; ETHYLPARABEN; METHYLPARABEN; HYDRATED SILICA; DIMETHICONE; BORON NITRIDE; MICROCRYSTALLINE WAX; PEG/PPG-20/23 DIMETHICONE; KAOLIN; HYDROGENATED COCO-GLYCERIDES; MAGNESIUM MYRISTATE; TRIBEHENIN; CETYL RICINOLEATE; PROPYLENE GLYCOL DICAPRYLATE/DICAPRATE; ISOPROPYL TITANIUM TRIISOSTEARATE

Active Ingredient

Octinoxate 6.3%....................

Titanium Dioxide 3.16%................

Purpose

.....Sunscreen

.....Sunscreen

Uses

• helps prevent sunburn

Warnings

For external use only

Do not use on damaged or broken skin

When using this product keep out of eyes. Rinse with water to remove.

Stop use and ask a doctor if rash occurs

Keep out of reach of children. If swallowed, get medical help or contact a Poison Control Center right away.

Directions

For sunscreen use:

• apply liberally 15 minutes before sun exposure

• children under 6 months of age: ask a doctor

• reapply at least every 2 hours

• use a water resistant sunscreen if swimming or sweating

• Sun Protection Measures. Spending time in the sun increases your risk of skin cancer and early skin aging. To decrease this risk, regularly use a sunscreen with a Broad Spectrum SPF value of 15 or higher and other sun protection measures including:

limit time in the sun, especially from 10 a.m.-2 p.m.
wear long-sleeved shirts, pants, hats, and sunglasses

Other information

• protect the product in this container from excessive heat and direct sun

INACTIVE INGREDIENT

Inactive Ingredients: PROPYLENE GLYCOL DICAPRYLATE/DICAPRATE, DIISOPROPYL DIMER DILINOLEATE, MICROCRYSTALLINE WAX/CIRE MICROCRISTALLINE, CALCIUM SODIUM BOROSILICATE, CETYL RICINOLEATE, HYDROGENATED COCO-GLYCERIDES, SILICA, TRIBEHENIN, POLYMETHYL METHACRYLATE, ETHYLENE/METHACRYLATE COPOLYMER, ETHYLPARABEN, METHYLPARABEN, MAGNESIUM MYRISTATE, HYDRATED SILICA, ALUMINA, DIMETHICONE, ISOPROPYL TITANIUM TRIISOSTEARATE, BORON NITRIDE, CETEARYL DIMETHICONE CROSSPOLYMER, CAPRYLYL METHICONE, PEG/PPG-20/23 DIMETHICONE, TRIETHOXYCAPRYLYLSILANE, KAOLIN. MAY CONTAIN: IRON OXIDES, TITANIUM DIOXIDE/CI 77891, MICA/CI 77019, BLUE 1 LAKE/CI 42090, BISMUTH OXYCHLORIDE/CI 77163

Questions or Comments?

Call toll free 1-800-FOR-AVON